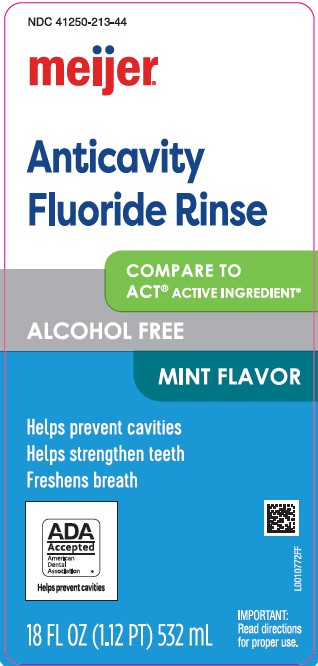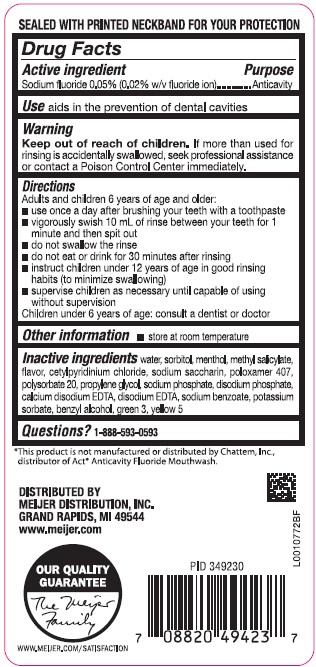 DRUG LABEL: Anticavity Fluoride Rinse
NDC: 41250-213 | Form: MOUTHWASH
Manufacturer: Meijer, Inc.
Category: otc | Type: HUMAN OTC DRUG LABEL
Date: 20260219

ACTIVE INGREDIENTS: SODIUM FLUORIDE 0.2 mg/1 mL
INACTIVE INGREDIENTS: WATER; SORBITOL; MENTHOL; METHYL SALICYLATE; CETYLPYRIDINIUM CHLORIDE; SACCHARIN SODIUM; POLOXAMER 407; POLYSORBATE 20; PROPYLENE GLYCOL; SODIUM PHOSPHATE; SODIUM PHOSPHATE, DIBASIC, ANHYDROUS; EDETATE CALCIUM DISODIUM; EDETATE DISODIUM ANHYDROUS; SODIUM BENZOATE; POTASSIUM SORBATE; BENZYL ALCOHOL; FD&C GREEN NO. 3; FD&C YELLOW NO. 5

Meijer 213.002/213AE rev 2
Anticavity Fluoride Rinse, Mint

Tamper Evident Statement

SEALED WITH PRINTED NECKBAND FOR YOUR PROTECTION

Active ingredient

Sodium fluoride 0.05% (0.02% w/v fluoride ion)

Purpose

Anticavity rinse

Use

aids in the prevention of dental cavities

Warning

for this product

Keep out of reach of children.

If more than used for rinsing is accidentally swallowed, seek professional assistance or contact a Poison Control Center immediately.

Directions

Adults and children 6 years of age and older:

- use once a day after brushing your teeth with a toothpaste
- vigorously swish 10 milliliters of rinse between your teeth for 1 minute and then spit out
- do not swallow the rinse
- do not eat or drink for 30 minutes after rinsing
- instruct children under 12 years of age in good rinsing habits (to minimize swallowing)
- supervise children as necessary until capable of using without supervision

Children under 6 years of age: consult a dentist or doctor

Other information

- store at room temperature

Inactive ingredients

water, sorbitol, menthol, methyl salicylate, flavor, cetylpyridinium chloride, sodium saccharin, poloxamer 407, polysorbate 20, propylene glycol, sodium phosphate, disodium phosphate, calcium disodium EDTA, disodium EDTA, sodium benzoate, potassium sorbate, benzyl alcohol, green 3, yellow 5

Questions?

1-888-593-0593

Disclaimer

*This product is not manufactured or distributed by Chattem, Inc., distributor of ActAnticavity Fluoride Mouthwash.

Adverse Reactions

DISTRIBUTED BY

MEIJER DISTRIBUTION, INC.

GRAND RAPIDS, MI 49544

www.meijer.com

OUR QUALITY GUARANTEE

WWW.MEIJER.COM/SATISFACTION

PID 349230

Principal display panel

NDC 41250-213-44

meijer®

Anticavity Fluoride Rinse

COMPARE TO ACT® ACTIVE INGREDIENT*

Alcohol Free

MINT FLAVOR

Helps prevent cavities

Helps strengthen teeth

Freshens breath

ADA Accepted

American Dental Association

Helps prevent cavities

IMPORTANT: Read directions for proper use.

18 FL OZ (1.12 pt) 532 mL